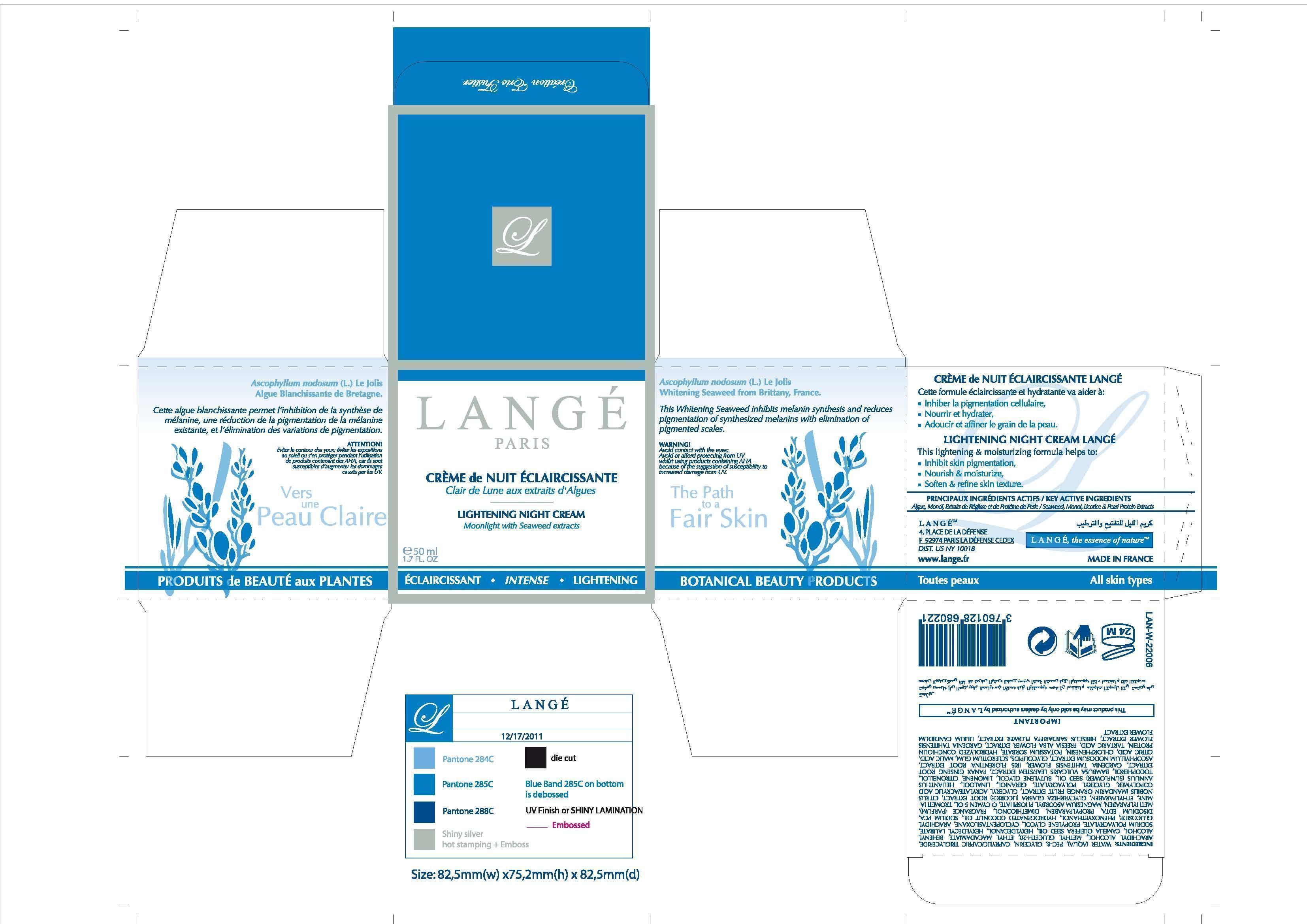 DRUG LABEL: Lightening Night Cream
NDC: 51830-020 | Form: CREAM
Manufacturer: LANGE SAS
Category: otc | Type: HUMAN OTC DRUG LABEL
Date: 20120718

ACTIVE INGREDIENTS: ETHYL MACADAMIATE 1 mg/50 mg
INACTIVE INGREDIENTS: WATER; POLYETHYLENE GLYCOL 400; GLYCERIN; MEDIUM-CHAIN TRIGLYCERIDES; ARACHIDYL ALCOHOL; METHYL GLUCETH-20; DOCOSANOL; CAMELLIA KISSII SEED OIL; HEXYLDECANOL; HEXYLDECYL LAURATE; SODIUM POLYACRYLATE (2500000 MW); PROPYLENE GLYCOL; CYCLOMETHICONE 5; ARACHIDYL GLUCOSIDE; PHENOXYETHANOL; HYDROGENATED COCONUT OIL; SODIUM PYRROLIDONE CARBOXYLATE; EDETATE DISODIUM; PROPYLPARABEN; DIMETHICONOL (100000 CST); METHYLPARABEN; MAGNESIUM ASCORBYL PHOSPHATE; O-CYMEN-5-OL; TROMETHAMINE; ETHYLPARABEN; GLYCYRRHIZA GLABRA; TANGERINE; ACRYLIC ACID; SUNFLOWER OIL; BUTYLENE GLYCOL; TOCOPHEROL; BAMBUSA VULGARIS TOP; ASIAN GINSENG; GARDENIA TAITENSIS FLOWER; IRIS GERMANICA VAR. FLORENTINA ROOT; ASCOPHYLLUM NODOSUM

KEY ACTIVE INGREDIENTS
Seaweed, Monoi, Licorice and Pearl Protein Extracts

PURPOSE

LIGHTENING NIGHT CREAM LANGE
This lightening and moisturizing formula helps to:
Inhibit skin pigmentation,
Nourish and moisturize,
Soften and refine skin texture.

Keep out of reach of children.

INDICATIONS AND USAGE

This Whitening Seaweed inhibits melanin synthesis and reduces pigmentation of synthesized melanins with elimination of pigmented scales.

WARNING!
Avoid contact with the eyes;
Avoid or afford protecting from UV
whilst using products containing AHA
because of the suggestion of susceptibility to
increased damage from UV.

DOSAGE AND ADMINISTRATION

50 ml
1.7 FL. OZ

INACTIVE INGREDIENT

WATER
PEG-8
GLYCERIN
CAPRYLIC/CAPRIC TRIGLYCERIDE
ARACHIDYL ALCOHOL
METHYL GLUCETH-20
ETHYL MACADAMIATE
BEHENYL ALCOHOL
CAMELLIA KISSI SEED OIL
HEXYLDECANOL
HEXYLDECYL LAURATE
SODIUM POLYACRYLATE
PROPYLENE GLYCOL
CYCLOPENTASILOXANE
ARACHIDYL GLUCOSIDE
PHENOXYETHANOL
HYDROGENATED COCONUT OIL
SODIUM PCA
DISODIUM EDTA
PROPYLPARABEN
DIMETHICONOL
METHYLPARABEN
MAGNESIUM ASCORBYL PHOSPHATE
o-CYMEN-5-OL
TROMETHAMINE
ETHYLPARABEN
GLYCYRRHIZA GLABRA (LICORICE) ROOT EXTRACT
CITRUS NOBILIS (MANDARIN ORANGE) FRUIT EXTRACT
GLYCERYL ACRYLATE/ACRYLIC ACID COPOLYMER
HELIANTHUS ANNUUS (SUNFLOWER) SEED OIL
BUTYLENE GLYCOL
TOCOPHEROL
GLYCERYL POLYACRYLATE
BAMBUSA VULGARIS EXTRACT
PANAX GINSENG ROOT EXTRACT
GARDENIA TAHITENSIS FLOWER
IRIS FLORENTINA ROOT EXTRACT
ASCOPHYLLUM NODOSUM EXTRACT

PACKAGE LABEL

LANGE
PARIS
LIGHTENING NIGHT CREAM
Moonlight with Seaweed extracts
50 ml
1.7 FL. OZ